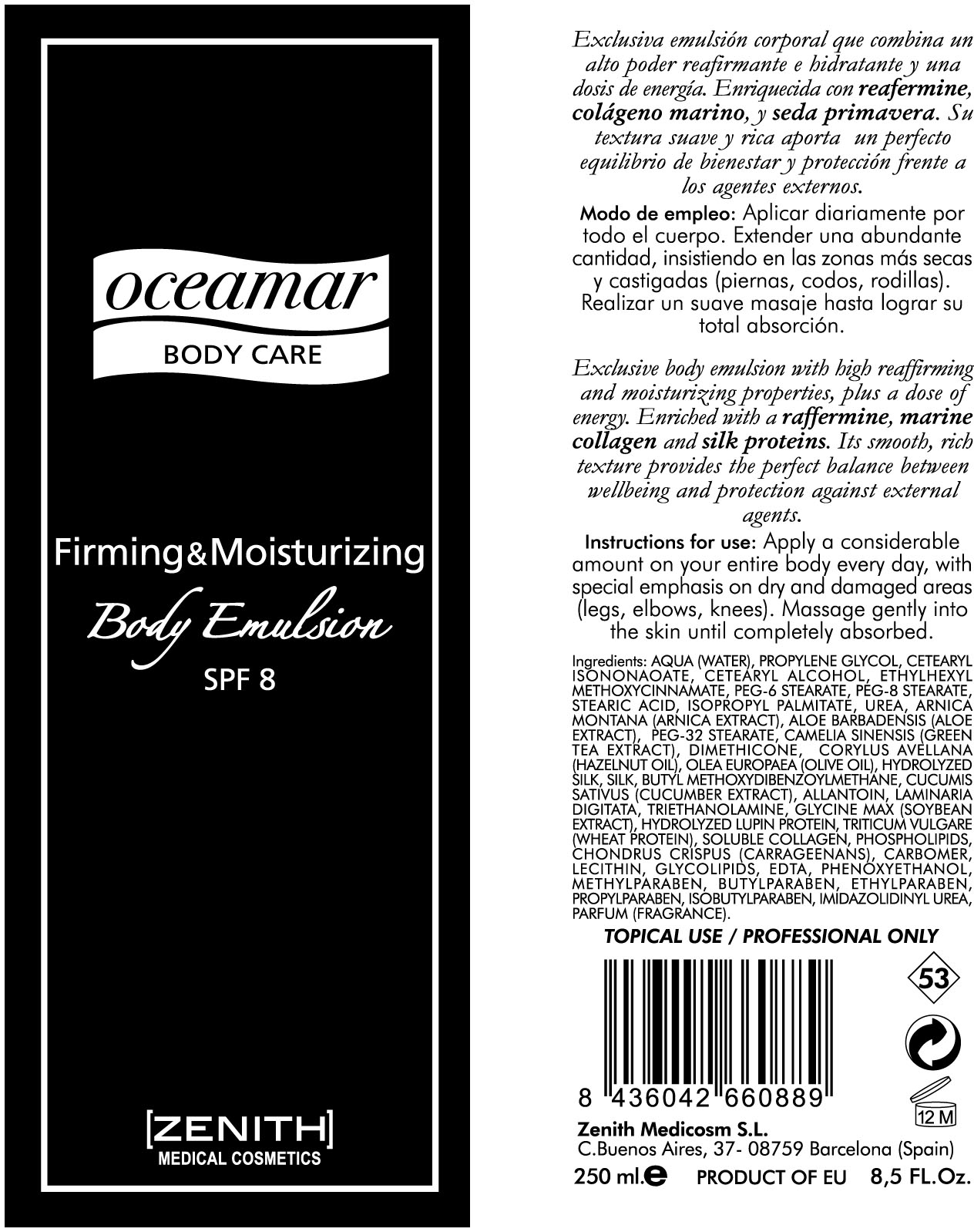 DRUG LABEL: FIRMING AND MOISTURIZING
NDC: 42248-132 | Form: EMULSION
Manufacturer: Zenith Medicosm SL
Category: otc | Type: HUMAN OTC DRUG LABEL
Date: 20120523

ACTIVE INGREDIENTS: OCTINOXATE 18.75 mL/250 mL
INACTIVE INGREDIENTS: ALOE VERA LEAF; PROPYLPARABEN; METHYLPARABEN; GREEN TEA LEAF; PEG-8 STEARATE; TROLAMINE; WATER; PROPYLENE GLYCOL; STEARIC ACID; PEG-6 STEARATE; ISOPROPYL PALMITATE; LAMINARIA DIGITATA; HYDROLYZED WHEAT PROTEIN (ENZYMATIC, 3000 MW); GREEN TEA LEAF; CETEARYL ISONONANOATE; SOYBEAN; CHONDRUS CRISPUS; CARBOMER HOMOPOLYMER TYPE B/C (ALLYL PENTAERYTHRITOL CROSSLINKED); METHYLPARABEN; ISOBUTYLPARABEN; ALLANTOIN; PHENOXYETHANOL; BUTYLPARABEN; ETHYLPARABEN; CETOSTEARYL ALCOHOL; HYDROGENATED SOYBEAN LECITHIN; PEG-32 STEARATE; EUROPEAN HAZELNUT OIL; OLIVE OIL; EDETIC ACID; DIMETHICONE; CUCUMBER; UREA; ARNICA MONTANA; IMIDUREA; BOMBYX MORI FIBER ; FISH SKIN COLLAGEN, SOLUBLE

Drug Facts

Active Ingredient

Octinoxate 7.5%

Description

SUN CARE CREAM FOR BODY

SPF 25

MEDIUM PROTECTION

UVA - UVB - WATER RESISTANT

Body emulsion rich in anti-age ingredients. Its formula protects skin from UVB and UVA rays while moisturizing and reaffirming the skin (collagen, aloe vera, green tea). Easy o apply for even, translucent coverage. Water resistant.

150ml. 5Fl.Oz.

Warning

TOPICAL USE / PROFESSIONAL ONLY

Instructions for use

Apply a considerable amount on entire body every day, with special emphasis on dry and damaged areas (legs, elbows, knees). Massage gently into the skin until completely absorbed